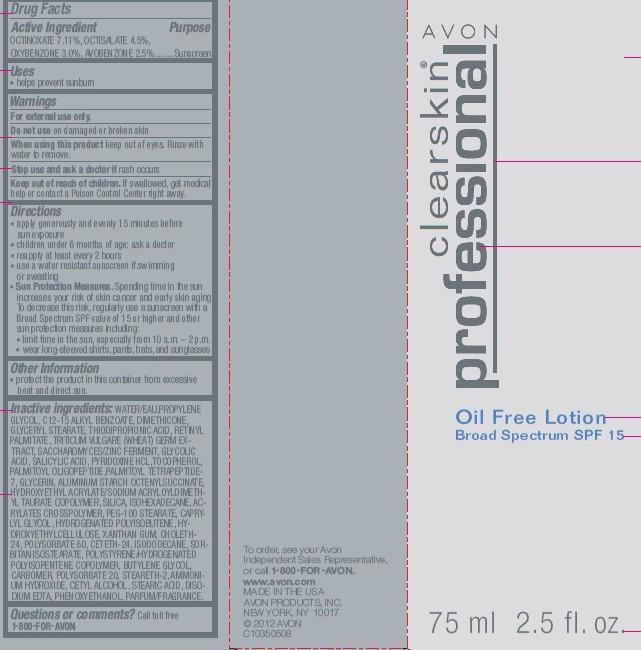 DRUG LABEL: Clearskin Professional
NDC: 10096-0185 | Form: LOTION
Manufacturer: New Avon LLC
Category: otc | Type: HUMAN OTC DRUG LABEL
Date: 20160211

ACTIVE INGREDIENTS: OCTINOXATE  71.1 mg/1 mL; OCTISALATE  45 mg/1 mL; OXYBENZONE  30 mg/1 mL; AVOBENZONE 25 mg/1 mL

Active Ingredient
OCTINOXATE 7.11%, OCTISALATE 4.5%,
OXYBENZONE 3.0%, AVOBENZONE 2.5%.......

Purpose

.....Sunscreen

Uses

- helps prevent sunburn

Warnings
For external use only.

Do not use on damaged or broken skin

When using this product keep out of eyes. Rinse with water to remove.

Stop use and ask a doctor if rash occurs

Keep out of reach of children. If swallowed, get medical help or contact a Poison Control Center right away.

Directions

- apply generously and evenly 15 minutes before sun exposure
- children under 6 months of age: ask a doctor reapply at least every 2 hours
- use a water resistant sunscreen if swimming or sweating
- Sun Protection Measures. Spending time in the sun increases your risk of skin cancer and early skin aging. To decrease this risk, regularly use a sunscreen with a Broad Spectrum SPF value of 15 or higher and other sun protection measures including:

- limit time in the sun, especially from 10 a.m. – 2 p.m.
- wear long-sleeved shirts, pants, hats, and sunglasses

Other Information

- protect the product in this container from excessive heat and direct sun.

INACTIVE INGREDIENT

Inactive ingredients: WATER/EAU,PROPYLENE GLYCOL, C12-15 ALKYL BENZOATE, DIMETHICONE, GLYCERYL STEARATE, THIODIPROPIONIC ACID, RETINYL PALMITATE, TRITICUM VULGARE (WHEAT) GERM EXTRACT, SACCHAROMYCES/ZINC FERMENT, GLYCOLIC ACID, SALICYLIC ACID, PYRIDOXINE HCL,TOCOPHEROL, PALMITOYL OLIGOPEPTIDE,PALMITOYL TETRAPEPTIDE- 7, GLYCERIN, ALUMINUM STARCH OCTENYLSUCCINATE, HYDROXYETHYL ACRYLATE/SODIUM ACRYLOYLDIMETHYL TAURATE COPOLYMER, SILICA, ISOHEXADECANE, ACRYLATES CROSSPOLYMER, PEG-100 STEARATE, CAPRYLYL GLYCOL, HYDROGENATED POLYISOBUTENE, HYDROXYETHYLCELLULOSE, XANTHAN GUM, CHOLETH-24, POLYSORBATE 60, CETETH-24, ISODODECANE, SORBITAN ISOSTEARATE, POLYSTYRENE/HYDROGENATED POLYISOPENTENE COPOLYMER, BUTYLENE GLYCOL, CARBOMER, POLYSORBATE 20, STEARETH-2, AMMONIUM HYDROXIDE, CETYL ALCOHOL, STEARIC ACID, DISODIUM EDTA, PHENOXYETHANOL, PARFUM/FRAGRANCE.

Questions or comments?

Call toll free 1-800-FOR-AVON